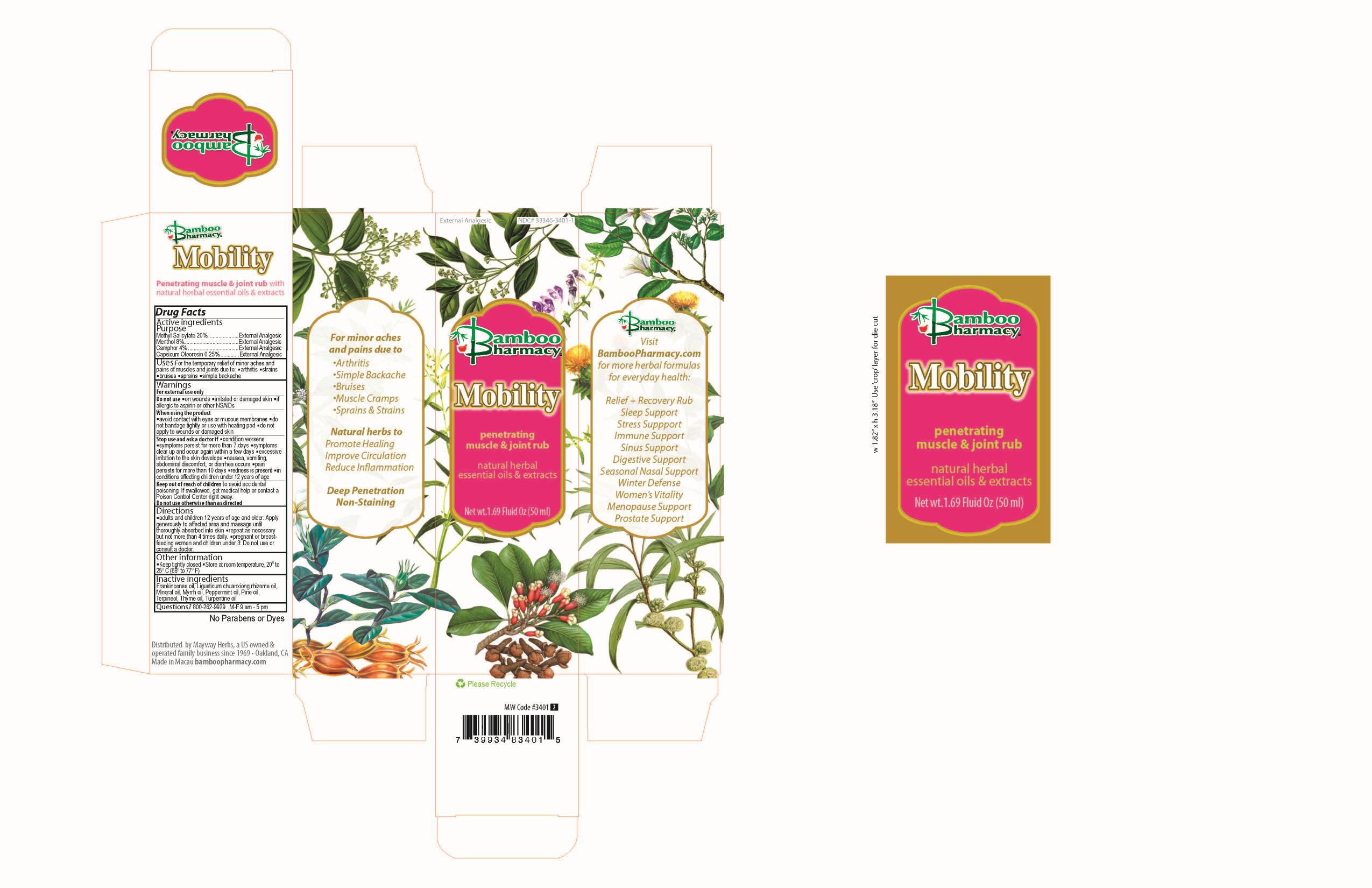 DRUG LABEL: Mobility
NDC: 33346-3401 | Form: OIL
Manufacturer: Mayway Corporation
Category: otc | Type: HUMAN OTC DRUG LABEL
Date: 20251223

ACTIVE INGREDIENTS: METHYL SALICYLATE 10 g/50 mL; MENTHOL 4 g/50 mL; CAMPHOR OIL 2 g/50 mL; CAPSICUM OLEORESIN 0.125 g/50 mL
INACTIVE INGREDIENTS: FRANKINCENSE OIL; MYRRH OIL; MINERAL OIL; PEPPERMINT OIL; PINE NEEDLE OIL (PINUS SYLVESTRIS); TERPINEOL; THYME OIL; TURPENTINE OIL; LIGUSTICUM SINENSE SUBSP. CHUANXIONG WHOLE

Mobility

Active ingredients

Active ingredients Purpose
Methyl Salicylate 20%..................................................External Analgesic
Menthol 8%..................................................................External Analgesic
Camphor 4% ...............................................................External Analgesic
Capsicum Oleoresin 0.25%..........................................External Analgesic

ASK DOCTOR

- condition worsens
- symptoms persist for more than 7 days
- symptoms clear up and occur again within a few days
- excessive irritation of the skin develops
- nausea, vomiting, abdominal discomfort, or diarrhea occurs
- pain persists for more than 10 days
- redness is present
- in conditions affecting children under 12 years of ageDo not use otherwise than as directed

Keep out of reach of children to avoid accidental poisoning.

If swallowed, get medical help or contact a Poison Control Center right away

Do not use otherwise than as directed

Directions

Pregnant or breastfeeding women and children under 3: Do not use or consult a doctor

Directions

- adults and children 12 years of age and older: Apply generously to the affected area and massage until thoroughly absorbed into skin

- repeat as necessary but not more than 4 times daily.

- pregnant or breastfeeding women and children under 3: Do not use or consult a doctor

Other information

- Keep tightly closed
- Store at room temperature, 20° to 25°C(68° to 77F)

Inactive ingredients

Frankincense oil, Ligusticum chuanxiong rhizome oil, Mineral Oil, Myrrh oil, Peppermint oil, Pine oil, Terpineol, Thyme oil, Turpentine oil

Questions?

+1-800-262-9929 M-F 9am - 5pm

Warnings

For external use only

Purpose

Active ingredients Purpose
Methyl Salicylate 20%..................................................External Analgesic
Menthol 8%..................................................................External Analgesic
Camphor 4% ...............................................................External Analgesic
Capsicum Oleoresin 0.25%..........................................External Analgesic

Do not use

- on wounds
- irritated or damaged skin
- if allergic to aspirin or other NSAIDs

When using this product

- avoid contact with the eyes or mucous membranes
- do not bandage tightly or use with heating pad
- do not apply to wounds or damaged skin

Stop use and ask a doctor if

- condition worsens
- symptoms persist for more than 7 days
- symptoms clear up and occur again within a few days
- excessive irritation of the skin develops
- nausea, vomiting, abdominal discomfort, or diarrhea occurs
- pain persists for more than 10 days
- redness is present
- in conditions affecting children under 12 years of age

Warnings

For external use only

Uses

For the temporary relief of minor aches and pains of muscles and joints due to:

- arthritis
- strains
- bruises
- sprains
- simple backache

Mobility Principal Display Panel